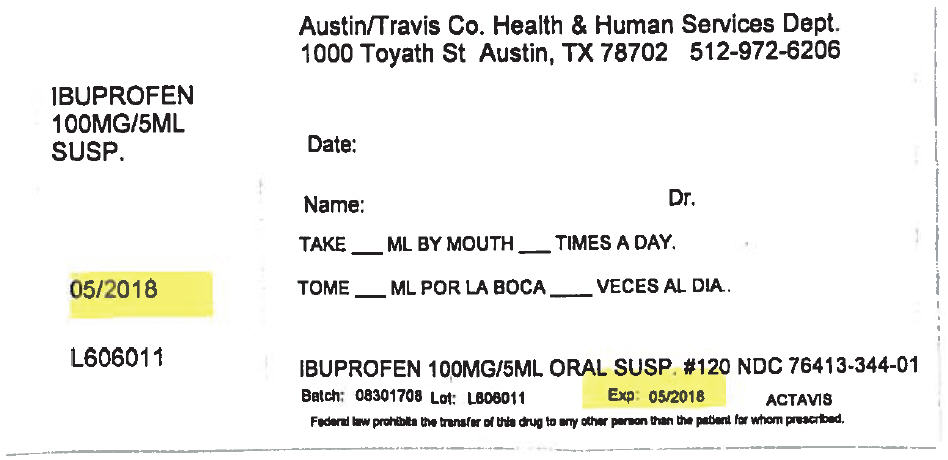 DRUG LABEL: Childrens Ibuprofen
NDC: 76413-344 | Form: SUSPENSION
Manufacturer: Central Texas Community Health Centers
Category: otc | Type: HUMAN OTC DRUG LABEL
Date: 20170908

ACTIVE INGREDIENTS: IBUPROFEN 100 mg/5 mL
INACTIVE INGREDIENTS: CITRIC ACID MONOHYDRATE; D&C YELLOW NO. 10; FD&C RED NO. 40; GLYCERIN; HYPROMELLOSE, UNSPECIFIED; POLYSORBATE 80; WATER; SODIUM BENZOATE; SUCROSE; XANTHAN GUM

Children's Ibuprofen Oral Suspension, USP

ACTIVE INGREDIENT

(in each 5 mL = 1 teaspoon)

Ibuprofen, USP 100 mg (NSAID)**

**nonsteroidal anti-inflammatory drug

PURPOSE

Pain reliever/fever reducer

USES

temporarily:

- relieves minor aches and pains due to the common cold, flu, sore throat, headache and toothache
- reduces fever

WARNINGS

Allergy alert: Ibuprofen may cause a severe allergic reaction, especially in people allergic to aspirin. Symptoms may include:

- hives
- shock
- asthma (wheezing)
- rash
- skin reddening
- blisters
- facial swelling

If an allergic reaction occurs, stop use and seek medical help right away.

Stomach bleeding warning: This product contains an NSAID, which may cause severe stomach bleeding. The chance is higher if your child:

- has had stomach ulcers or bleeding problems
- takes a blood thinning (anticoagulant) or steroid drug
- takes other drugs containing prescription or nonprescription NSAIDs (aspirin, ibuprofen, naproxen, or others)
- takes more or for a longer time than directed

Sore throat warning: Severe or persistent sore throat or sore throat accompanied by high fever, headache, nausea, and vomiting may be serious. Consult doctor promptly. Do not use more than 2 days or administer to children under 3 years of age unless directed by doctor.

DO NOT USE

- if the child has ever had an allergic reaction to any other pain reliever/fever reducer
- right before or after heart surgery

ASK DOCTOR BEFORE USE IF

- stomach bleeding warning applies to your child
- child has a history of stomach problems, such as heartburn
- child has problems or serious side effects from taking pain relievers or fever reducers
- child has not been drinking fluids
- child has lost a lot of fluid due to vomiting or diarrhea
- child has high blood pressure, heart disease, liver cirrhosis, or kidney disease
- child has asthma
- child is taking a diuretic

ASK DOCTOR OR PHARMACIST BEFORE USE IF THE CHILD IS

- under a doctor's care for any serious condition
- taking any other drug

WHEN USING THIS PRODUCT

- take with food or milk if stomach upset occurs
- the risk of heart attack or stroke may increase if you use more than directed or for longer than directed

STOP USE AND ASK A DOCTOR IF

- child experiences any of the following signs of stomach bleeding

- feels faint
- vomits blood
- has bloody or black stools
- has stomach pain that does not get better

- the child does not get any relief within the first day (24 hours) of treatment
- fever or pain gets worse or lasts more than 3 days
- redness or swelling is present in the painful area
- any new symptoms appear

KEEP OUT OF REACH OF CHILDREN

In case of overdose, get medical help or contact a Poison Control Center right away (1-800-222-1222).

DIRECTIONS

- this product does not contain directions or complete warnings for adult use
- do not give more than directed
- shake well before using
- find right dose on chart. If possible, use weight to dose; otherwise use age.
- use only enclosed measuring cup
- if needed, repeat dose every 6-8 hours
- do not use more than 4 times a day
- replace original bottle cap to maintain child resistance

Dosing Chart
Weight (lb) | Age (yr) | Dose (tsp or mL)
under 2 years |  | ask a doctor
24 – 35 lbs | 2 – 3 years | 1 tsp or 5 mL
36 – 47 lbs | 4 – 5 years | 1½ tsp or 7.5 mL
48 – 59 lbs | 6 – 8 years | 2 tsp or 10 mL
60 – 71 lbs | 9 – 10 years | 2½ tsp or 12.5 mL
72 – 95 lbs | 11 years | 3 tsp or 15 mL

Other information

- each teaspoon contains: sodium 2 mg
- do not use if printed neckband is broken or missing
- store between 20 - 25°C (68 - 77°F)
- see bottom panel for lot number and expiration date

INACTIVE INGREDIENT

Berry flavor: citric acid, D&C yellow #10, FD&C red #40, flavors, glycerin, hypromellose, polysorbate 80, purified water, sodium benzoate, sucrose, xanthan gum

Dye free berry flavor: citric acid, flavors, glycerin, hypromellose, polysorbate-80, purified water, sodium benzoate, sucrose, xanthan gum

Bubble gum flavor: artificial bubble gum flavor, citric acid, FD&C red #40, glycerin, hypromellose, polysorbate 80, purified water, sodium benzoate, sucrose, xanthan gum.

QUESTIONS?

1-800-432-8534 between 9 am and 4 pm EST, Monday – Friday.

PRINCIPAL DISPLAY PANEL - 100 MG/5 ML Bottle Label

Austin/Travis Co. Health & Human Services Dept.
1000 Toyath St Austin, TX 78702 512-972-6206

IBUPROFEN
100MG/5ML
SUSP.

Date:

Name:
Dr.

TAKE ___ ML BY MOUTH ___ TIMES A DAY.

05/2018

L606011

IBUPROFEN 100MG/5ML ORAL SUSP. #120 NDC 76413-344-01

Batch: 08301708
Lot: L606011
Exp: 05/2018
ACTAVIS

Federal law prohibits the transfer of this drug to any other person than the patient for whom prescribed.